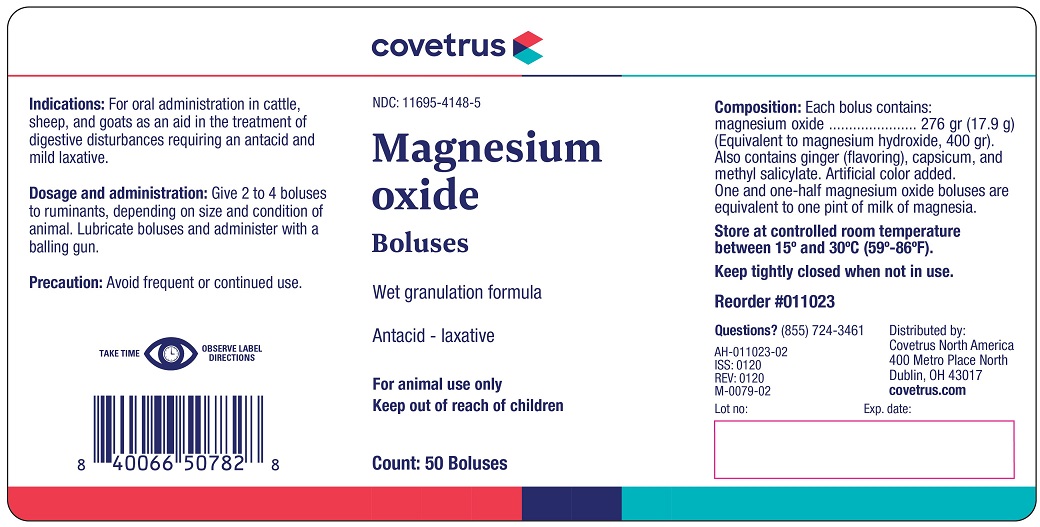 DRUG LABEL: Magnesium Oxide
NDC: 11695-4148 | Form: TABLET
Manufacturer: Covetrus North America
Category: animal | Type: OTC ANIMAL DRUG LABEL
Date: 20210105

ACTIVE INGREDIENTS: MAGNESIUM OXIDE 17.9 g/1 1
INACTIVE INGREDIENTS: SODIUM STARCH GLYCOLATE TYPE A CORN; MAGNESIUM STEARATE; STARCH, CORN; WATER

Magnesium oxide

INDICATIONS AND USAGE

Wet granulation formula

Antacid - laxative

For animal use only

Keep out of reach of children

Indications:

For oral administration in cattle, sheep and goats as a aid in the treatment of digestive disturbances requiring and antacid and mild laxative.

Dosage and administration

Give 2 to 4 boluses to ruminants, depending on size and condition of animal. Lubricate boluses and administer with a balling gun.

Precaution

Avoid frequent or continued use.

TAKE TIME OBSERVE LABEL DIRECTIONS

Composition

Each bolus contains:

magnesium oxide ......................... 276 gr (17.9 g)

(Equivalent to magnesium hydroxide3, 400 gr.).

Also contains ginger (flavoring), capsicum, and methyl salicylate. Artificial color added.

One and one-half magnesium boluses are equivalent to one pint of milk of magnesia.

STORAGE AND HANDLING

Store at controlled room temperature between 15° and 30°C (59°-86°F).

Keep tightly closed when not in use.